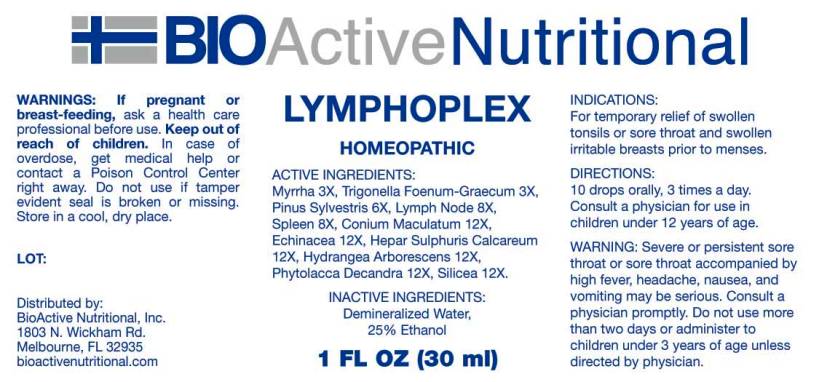 DRUG LABEL: Lymphoplex
NDC: 43857-0294 | Form: LIQUID
Manufacturer: BioActive Nutritional, Inc.
Category: homeopathic | Type: HUMAN OTC DRUG LABEL
Date: 20160420

ACTIVE INGREDIENTS: MYRRH 3 [hp_X]/1 mL; FENUGREEK SEED 3 [hp_X]/1 mL; PINUS SYLVESTRIS LEAFY TWIG 6 [hp_X]/1 mL; SUS SCROFA LYMPH 8 [hp_X]/1 mL; SUS SCROFA SPLEEN 8 [hp_X]/1 mL; CONIUM MACULATUM FLOWERING TOP 12 [hp_X]/1 mL; ECHINACEA ANGUSTIFOLIA 12 [hp_X]/1 mL; CALCIUM SULFIDE 12 [hp_X]/1 mL; HYDRANGEA ARBORESCENS ROOT 12 [hp_X]/1 mL; PHYTOLACCA AMERICANA ROOT 12 [hp_X]/1 mL; SILICON DIOXIDE 12 [hp_X]/1 mL
INACTIVE INGREDIENTS: WATER; ALCOHOL

Drug Facts:

ACTIVE INGREDIENTS:

Myrrha 3X, Trigonella foenum-graecum 3X, Pinus sylvestris 6X, Lymph (suis) 8X, Spleen (suis) 8X, Conium maculatum 12X, Echinacea (Angustifolia) 12X, Hepar sulphuris calcareum 12X, Hydrangea arborescens 12X, Phytolacca decandra 12X, Silicea 12X

INDICATIONS:

For temporary relief of swollen tonsils or sore throat and swollen irritable breasts prior to menses.

WARNINGS:

If pregnant or breast-feeding, ask a health care professional before use.

Keep out of reach of children. In case of overdose, get medical help or contact a Poison Control Center right away.

Do not use if tamper evident seal is broken or missing.

Store in a cool, dry place.

Keep out of reach of children. In case of overdose, get medical help or contact a Poison Control Center right away.

DIRECTIONS:

10 drops orally, 3 times a day. Consult a physician for use in children under 12 years of age.

WARNING: Severe or persistent sore throat or sore throat accompanied by high fever, headache, nausea, and vomiting may be serious. Consult a physician promptly. Do not use more than two days or administer to children under 3 years of age unless directed by a physician.

INDICATIONS:

For temporary relief of swollen tonsils or sore throat and swollen irritable breasts prior to menses.

INACTIVE INGREDIENTS:

Demineralized Water, 25% Ethanol.

QUESTIONS:

Distributed by:
BioActive Nutritional, Inc.
1803 N. Wickham Rd.
Melbourne, FL 32935
bioactivenutritional.com

PACKAGE LABEL DISPLAY:

BIOActive Nutritional

LYMPHOPLEX

HOMEOPATHIC

1 FL OZ (30 ml)